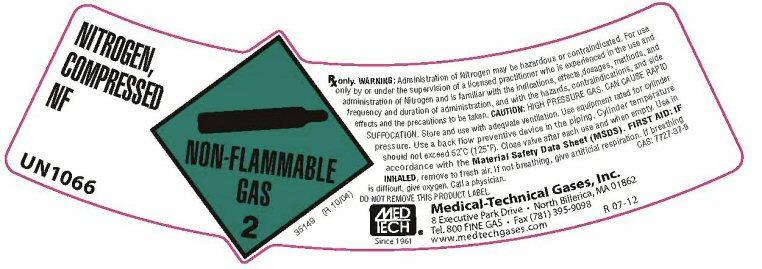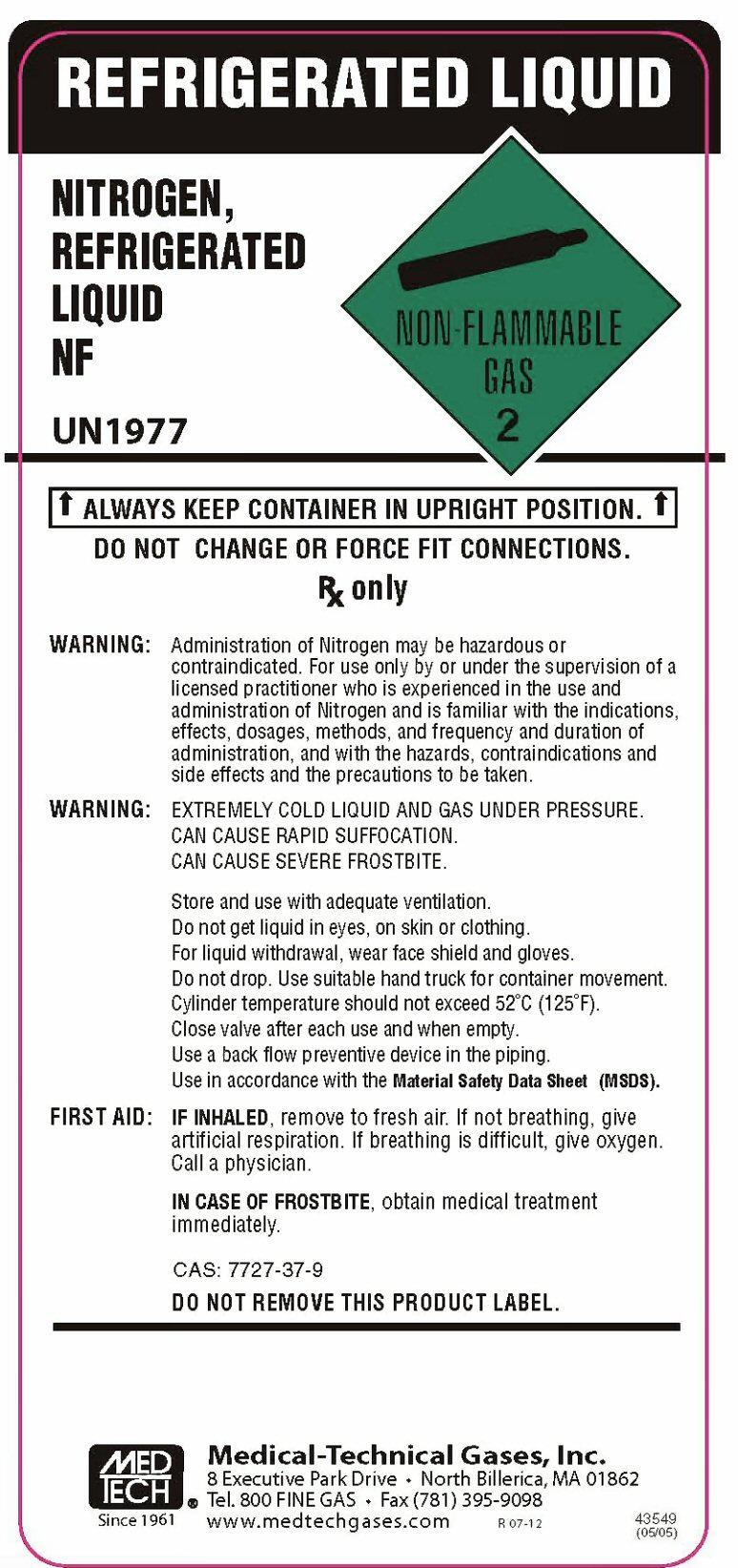 DRUG LABEL: NITROGEN
NDC: 10736-203 | Form: GAS
Manufacturer: Medical-Technical Gases, Inc.
Category: prescription | Type: HUMAN PRESCRIPTION DRUG LABEL
Date: 20251125

ACTIVE INGREDIENTS: NITROGEN 990 mL/1 L

Nitrogen

Nitrogen HP

NITROGEN COMPRESSED N.F. UN1066 NON-FLAMMABLE GAS 2

CAS No. 7727-37-9 N2

DO NOT REMOVE THIS LABEL

CAUTION: FEDERAL LAW PROHIBITS DISPENSING WITHOUT PRESCRIPTION.

CAUTION: HIGH PRESSURE GAS. CAN CAUSE RAPID SUFFOCATION (DUE TO OXYGEN DEFICIENCY)

WARNING: Administration of Nitrogen may be hazardous or contraindicated. For use only by or under the supervision
of a licensed practitioner who is experienced in the use and administration of Nitrogen and is familiar with the
indications, effects, dosages, methods, and frequency and duration of administration, and with the hazards,
contraindications, and side effects and the precautions to be taken.
CAUTION:Store and use with adequate ventilation. Use equipment rated for cylinder pressure. Cylinder temperature should
not exceed 125 degrees F (52 degrees C). Close valve tightly and replace cylinder cap when not in use and when empty. USE IN ACCORDANCE WITH MED-TECH'S MATERIAL SAFETY DATA SHEET.
FIRST AID: If inhaled, remove to fresh air. If not breathing, give artificial respiration. If breathing is difficult,
give oxygen. CALL A PHYSICIAN

1994

MED TECH Since 1961

Medical-Technical Gases, Inc. 20 Hall Street, Medford, MA 02155 800 fine gas FAX 781-395-9098

Nitrogen Liquid

REFRIGERATED LIQUID

NITROGEN REFRIGERATED LIQUID NF
NON-FLAMMABLE GAS 2
UN 1977

ALWAYS KEEP CONTAINER IN UPRIGHT POSITION.
DO NOT CHANGE OR FORCE FIT CONNECTIONS.
Rx only

WARNING:
Administration of Nitrogen may be hazardous or contraindicated. For use only by or under the supervision of a licensed practitioner who is experienced in the use and administration of Nitrogen and is familiar with the indications, effects, dosages, methods, and frequency and duration of administration, and with the hazards, contraindications and side effects and the precautions to be taken.
WARNING:
EXTREMELY COLD LIQUID AND GAS UNDER PRESSURE.
CAN CAUSE RAPID SUFFOCATION.
CAN CAUSE SEVERE FROSTBITE.
Store and use with adequate ventilation.
Do not get liquid in eyes, on skin, or clothing.
For liquid withdraw, wear face shield and gloves.
Do not drop. Use suitable hand truck for container movement.
Avoid spills. Do not walk on or roll equipment over spills.
Cylinder temperature should not exceed 52° C (125° F).
Close valve after each use and when empty.
Use a back flow preventive device in the piping.
Use in accordance with the Material Safety Data Sheet (MSDS).
FIRST AID: IF INHALED, remove to fresh air. If not breathing, give artificial respiration. If breathing is difficult, give oxygen. Call a physician.
IN CASE OF FROSTBITE, obtain medical treatment immediately.
CAS: 7727-37-9
DO NOT REMOVE THIS PRODUCT LABEL.

MED TECH Since 1961 Medical-Technical Gases, Inc. 8 Executive Park drive North Bilerica, MA 01862

Tel. 800 FINE GAS Fax (781) 395-9098 www.medtechgases.com R 07-12 43549 (05/05)